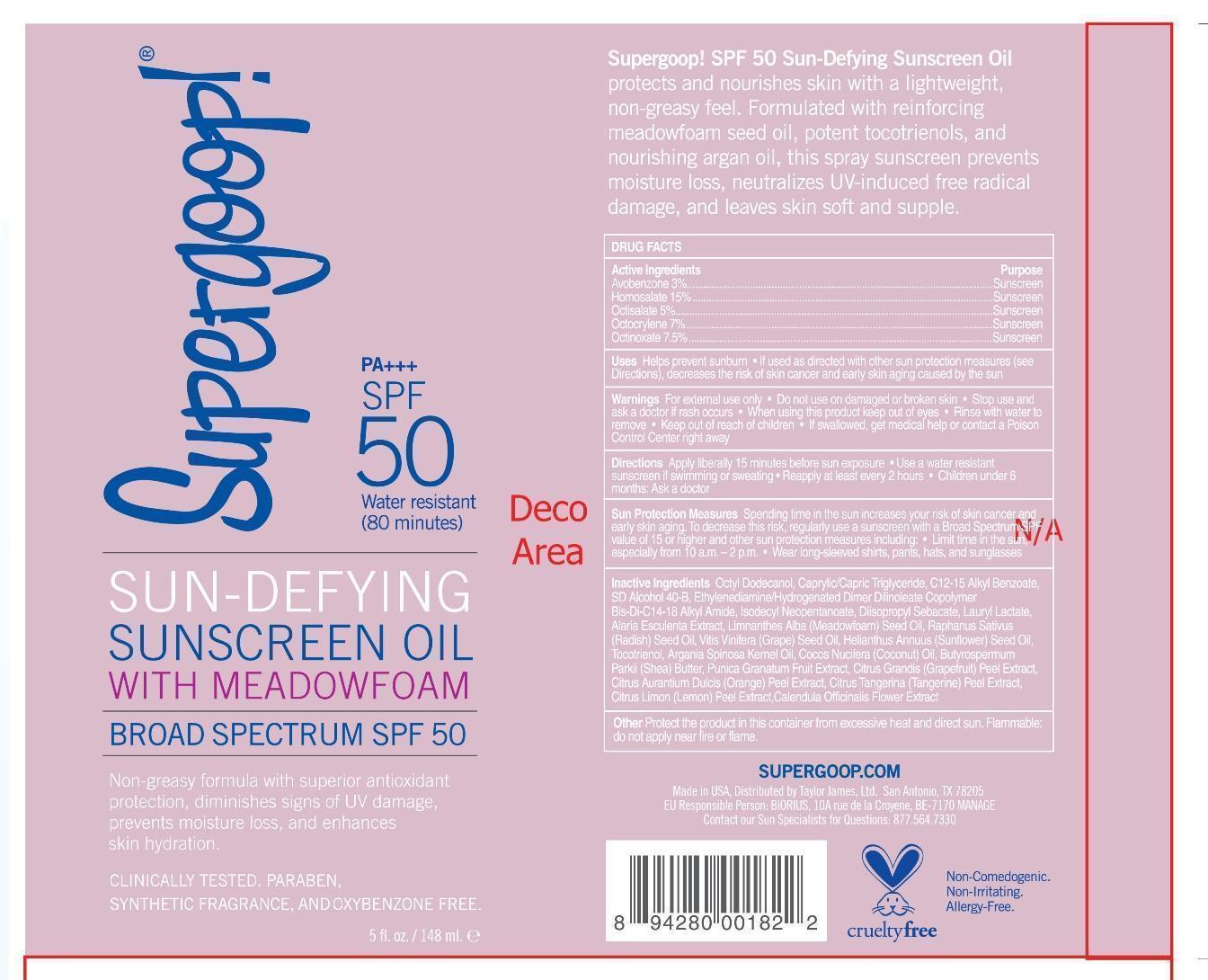 DRUG LABEL: Sun-Defying Sunscreen Oil Broad Spectrum SPF 50

NDC: 75936-125 | Form: OIL
Manufacturer: TAYLOR JAMES, LTD.
Category: otc | Type: HUMAN OTC DRUG LABEL
Date: 20201112

ACTIVE INGREDIENTS: AVOBENZONE 3 g/100 mL; HOMOSALATE 15 g/100 mL; OCTISALATE 5 g/100 mL; OCTOCRYLENE 7 g/100 mL; OCTINOXATE 7.5 g/100 mL
INACTIVE INGREDIENTS: OCTYLDODECANOL; MEDIUM-CHAIN TRIGLYCERIDES; ALKYL (C12-15) BENZOATE; ISODECYL NEOPENTANOATE; DIISOPROPYL SEBACATE; LAURYL LACTATE; ALARIA ESCULENTA; MEADOWFOAM SEED OIL; GRAPE SEED OIL; SUNFLOWER OIL; TOCOTRIENOLS; ARGAN OIL; COCONUT OIL; SHEA BUTTER; POMEGRANATE; GRAPEFRUIT PEEL; ORANGE PEEL; TANGERINE PEEL; LEMON PEEL; CALENDULA OFFICINALIS FLOWER

Sun-Defying Sunscreen Oil

Active Ingredients Purpose

Avobenzone 3% Sunscreen

Homosalate 15% Sunscreen

Octisalate 5% Sunscreen

Octocrylene 7% Sunscreen

Octinoxate 7.5 % Sunscreen

Uses
· helps prevent sunburn
· If used as directed with other sun protection measures (see Directions),
decreases the risk of skin cancer and early skin aging caused by the sun

Keep out of reach of children

If swallowed, get medical help or contact a Poison Control Center right away.

Stop use and ask a doctor if rash occurs

Warnings

· For external use only
· Do not use on damaged or broken skin
· When using this product keep out of eyes. Rinse with water to remove.

Directions
· Apply liberally 15 minutes before sun exposure
· Use a water resistant sunscreen if swimming or sweating

· Reapply at least every 2 hours

· Children under 6 months: Ask a doctor
· Sun Protection Measures. Spending time in the sun increases your risk of skin
cancer and early skin aging. To decrease this risk, regularly use a sunscreen
with broad spectrum SPF of 15 or higher and other sun protection measures
including:
· limit time in the sun, especially from 10 a.m. - 2 p.m.
· wear long-sleeve shirts, pants, hats, and sunglasses

INACTIVE INGREDIENT

Octyl Dodecanol, Caprylic/Capric Triglyceride, C12-15 Alkyl Benzoate, SD Alcohol 40-B, Ethylenediamine/Hydrogenated Dimer Dilinoleate Copolymer Bis-Di-C14-18 Alkyl Amide, Isodecyl Neopentanoate, Diisopropyl Sebacate, Lauryl Lactate, Alaria Esculenta Extract, Limnanthes Alba (Meadowfoam) Seed Oil, Raphanus Sativus (Radish) Seed Oil, Vitis Vinifera (Grape) Seed Oil, Helianthus Annuus (Sunflower) Seed Oil, Tocotrienol, Argania Spinosa Kernel Oil, Cocos Nucifera (Coconut) Oil, Butyrospermum Parkii (Shea) Butter, Punica Granatum Fruit Extract, Citrus Grandis (Grapefruit) Peel Extract, Citrus Aurantium Dulcis (Orange) Peel Extract, Citrus Tangerina (Tangerine) Peel Extract, Citrus Limon (Lemon) Peel Extract, Calendula Officinalis Flower Extract

PACKAGE LABEL

Supergoop!

Sun-Defying Sunscreen oil with Meadowfoam

Broad Spectrum SPF 50

5 Fl. Oz. / 148 ml